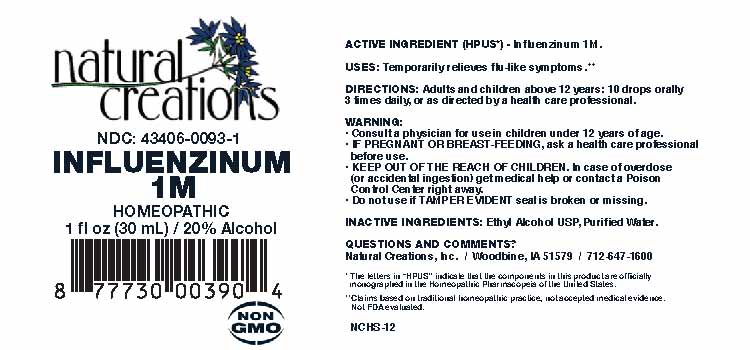 DRUG LABEL: Influenzinum
NDC: 43406-0093 | Form: LIQUID
Manufacturer: Natural Creations, Inc
Category: homeopathic | Type: HUMAN OTC DRUG LABEL
Date: 20251216

ACTIVE INGREDIENTS: INFLUENZA A VIRUS A/SINGAPORE/GP1908/2015 IVR-180 (H1N1) WHOLE 1 [hp_M]/1 mL; INFLUENZA A VIRUS A/NORTH CAROLINA/04/2016 (H3N2) WHOLE 1 [hp_M]/1 mL; INFLUENZA B VIRUS B/IOWA/06/2017 WHOLE 1 [hp_M]/1 mL; INFLUENZA B VIRUS B/SINGAPORE/INFTT-16-0610/2016 WHOLE 1 [hp_M]/1 mL
INACTIVE INGREDIENTS: ALCOHOL; WATER

INFLUENZINUM 1M

ACTIVE INGREDIENT (HPUS*): Inlfuenzinum 1M.

INDICATIONS AND USAGE

USES: Temporarily relieves flu-like symptoms.**

PURPOSE

USES: Temporarily relieves flu-like symptoms.**

DOSAGE AND ADMINISTRATION

DIRECTIONS: Adults and children above 12 years: 10 drops orally 1 time a month or as directed by a health care professional.

KEEP OUT OF REACH OF CHILDREN

KEEP OUT OF THE REACH OF CHILDREN. In case of overdose (or accidental ingestion) get medical help or contact a Poison Control Center right away.

WARNINGS:

- Consult a physician for use in children under 12 years of age.
- IF PREGNANT OR BREAST-FEEDING, ask a health care professional before use.
- KEEP OUT OF THE REACH OF CHILDREN. In case of overdose (or accidental ingestion) get medical help or contact a Poison Control Center right away.
- Do not use if TAMPER EVIDENT seal is broken or missing.

INACTIVE INGREDIENTS: Ethyl Alcohol USP, Purified Water.

QUESTIONS & COMMENTS?

Natural Creations, Inc. / Woodbine, IA 51579 / 712-647-1600

REFERENCES

*The letters "HPUS" indicate the component in this product is officially monographed in the Homeopathic Pharmacopeia of the United States.

**Claims based on traditional homeopathic practice, not accepted medical evidence. Not FDA evaluated.

PACKAGE LABEL

NDC: 43406-0093-1

INFLUENZINUM 1M

HOMEOPATHIC

1 fl oz (30 mL) / 20% Alcohol